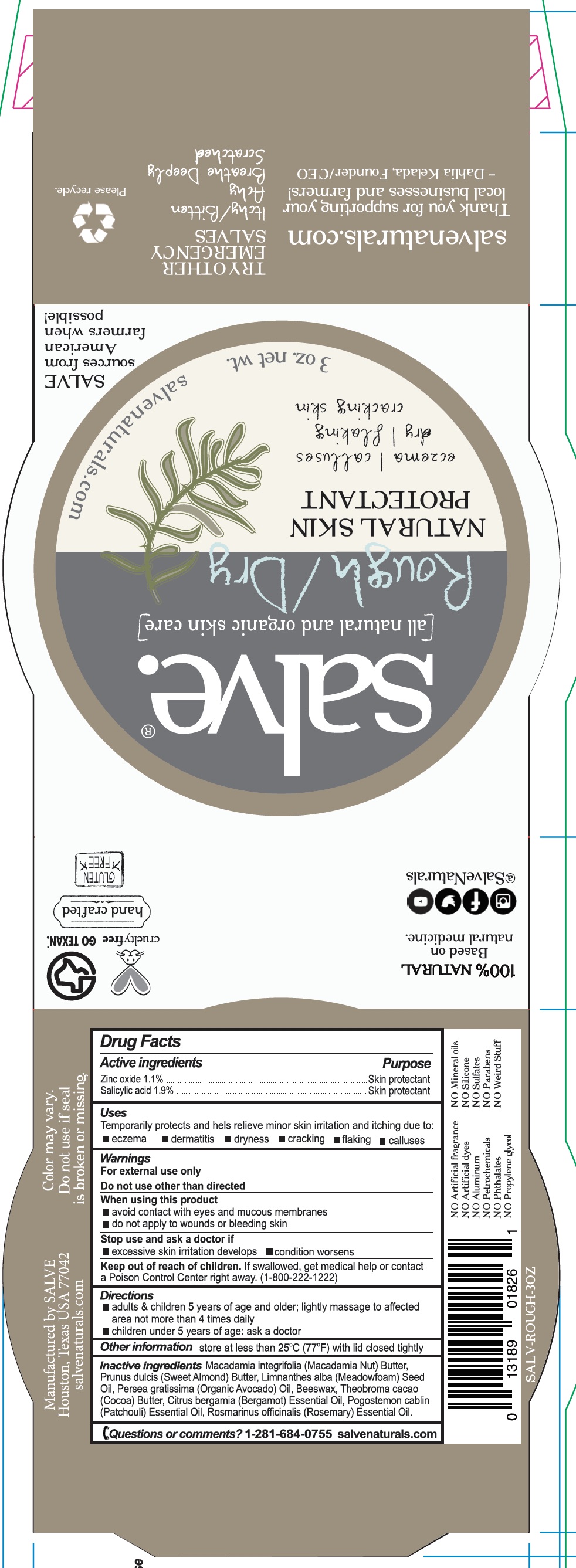 DRUG LABEL: Rough Dry
NDC: 71157-0020 | Form: CREAM
Manufacturer: Kelada Creative Group LLC DBA SALVE
Category: otc | Type: HUMAN OTC DRUG LABEL
Date: 20171016

ACTIVE INGREDIENTS: ZINC OXIDE 8 g/90 mL
INACTIVE INGREDIENTS: SALICYLIC ACID 15 g/90 mL; WHITE WAX; COCOA BUTTER; ROSEMARY OIL; PATCHOULI OIL; BERGAMOT OIL; MEADOWFOAM SEED OIL; ALMOND; AVOCADO OIL; HYDROGENATED MACADAMIA SEED OIL

Rough/Dry

ACTIVE INGREDIENT

Zinc oxide 1.1%

PURPOSE

Temporarily protects and helps relieve minor skin irritation and itching due to eczema, dermatitis, dryness, cracking, flaking, and calluses.

WARNINGS

For external use only

Do not use other than as directed

When using this product

- avoid contact with eyes and mucous membranes
- do not apply to wounds or bleeding skin

DOSAGE AND ADMINISTRATION

Temporarily protects and helps relieve minor skin irritation and itching due to eczema, dermatitis, dryness, cracking, flaking, and calluses.

Keep out of reach of children. If swallowed, get medical help or contact a Poison Control Center right away.

INACTIVE INGREDIENT

Salicylic acid, Macadamia nut butter, Sweet almond butter, Meadowfoam seed oil, Organic avocado oil, Beeswax, Cocoa butter, Bergamot essential oil, Patchouli essential oil, Rosemary essential oil

INDICATIONS AND USAGE

Temporarily protects and helps relieve minor skin irritation and itching due to eczema, dermatitis, dryness, cracking, flaking, and calluses.